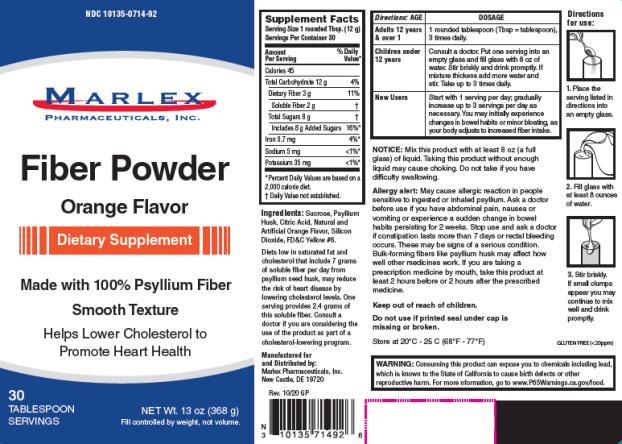 DRUG LABEL: Psyllium Fiber
NDC: 10135-714 | Form: POWDER
Manufacturer: Marlex Pharmaceuticals Inc
Category: other | Type: DIETARY SUPPLEMENT
Date: 20201027

ACTIVE INGREDIENTS: PSYLLIUM HUSK 2.4 g/12 g
INACTIVE INGREDIENTS: SUCROSE; CITRIC ACID MONOHYDRATE; SILICON DIOXIDE; FD&C YELLOW NO. 6

Psyllium Fiber Powder

Supplement Facts

Serving Size: 1 rounded Tbsp. (12 g)

Servings per container: 30

Amount per serving % Daily Value

Calories 45

Total Carbohydrate 12 g 4%*

Dietary Fiber 3 g 11%*

Soluble fiber 2 g ϯ

Total sugar 8 g ϯ

Includes 8 g Added Sugars 16%*

Iron 0.7 mg 4%*

Sodium 5 mg < 1%*

Potassium 35 mg < 1%*

*Percent Daily Values are based on a 2,000 calorie Diet

ϯ Daily Value not established.

Diets low in saturated fat and cholesterol that include 7 grams of soluble fiber per day from Psyllium seed husk, may reduce the risk of heart disease by lowering cholesterol levels. One serving provides 2.4 grams of this soluble fiber. Consult a doctor if you are considering the Use of the product as part of a cholesterol-lowering program.

Directions:

Adults 12 years & over 1: 1 rounded tablespoon (Tbsp = tablespoon), 3 times daily

Children under 12 years: Consult a doctor. Put one serving into an empty glass and fill glass with 8 oz of water. Stir briskly and drink promptly. If mixture thickens, add more water and stir. Take up to 3 times daily

New Users: Start with 1 serving per day; gradually increase up to 3 servings per day as necessary. You may initially experience changes in bowel habits or minor bloating, as your body adjusts to increased fiber intake.

NOTICE: Mix this product with at least 8 oz (a full glass) of liquid. Taking this product without enough liquid may cause choking. Do not take if you have difficulty swallowing.

Allergy alert: May cause allergic reaction in people sensitive to ingested or inhaled psyllium. Ask a doctor before use if you have abdominal pain, nausea or vomiting or experience a sudden change in bowel habits persisting for 2 weeks.

Stop use and ask a doctor if constipation lasts more than 7 days or rectal bleeding occurs. These may be signs of a serious condition.

Bulk-forming fibers like psyllium husk may affect how well other medicines work. If you are taking a prescription medicine by mouth, take this product at least 2 hours before or 2 hours after the prescribed medicine.

Keep out of reach of children.

Do not use if printed seal under cap is missing or broken.

Store at 20°C - 25 C (68°F - 77°F)

WARNING:

Consuming this product can expose you to chemicals including lead, which is known to the State of California to cause birth defects or other reproductive harm. For more information, go to www.P65Warnings.ca.gov/food.

Ingredients: Sucrose, Psyllium Husk, Citric Acid, Natural and Artificial Orange Flavor, Silicon Dioxide, FD&C Yellow #6.

Manufactured for and Distributed by:

Marlex Pharmaceuticals, Inc.

New Castle, DE 19720

Rev. 10/20 GP

PRINCIPAL DISPLAY PANEL

NDC 10135-0714-92
Marlex Pharmaceuticals
Psyllium Fiber Powder
Orange Flavor
368 g (13 oz)

Revised: 10/2020

Document Id: 702fbfb7-cb08-4fda-a344-9c913f35bed1

58476-3

Set id: afa81aad-6ada-4275-9946-e9fceb62bfe9

Version: 1

Effective Time: 20201006

Marlex Pharmaceuticals, Inc.